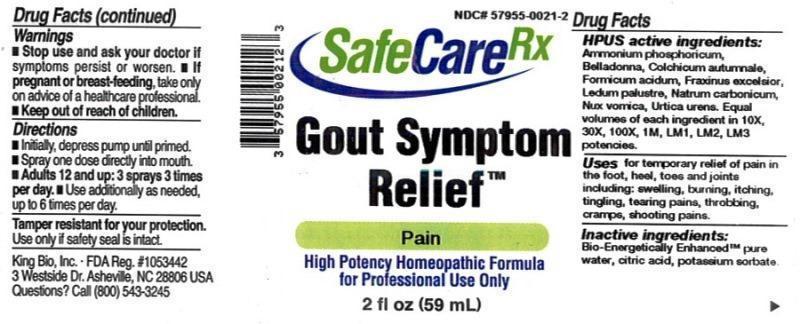 DRUG LABEL: Gout Symptom Relief
NDC: 57955-0021 | Form: LIQUID
Manufacturer: King Bio Inc.
Category: homeopathic | Type: HUMAN OTC DRUG LABEL
Date: 20150310

ACTIVE INGREDIENTS: AMMONIUM PHOSPHATE, DIBASIC 10 [hp_X]/59 mL; ATROPA BELLADONNA 10 [hp_X]/59 mL; COLCHICUM AUTUMNALE BULB 10 [hp_X]/59 mL; FORMIC ACID 10 [hp_X]/59 mL; FRAXINUS EXCELSIOR BARK 10 [hp_X]/59 mL; FRAXINUS EXCELSIOR LEAF 10 [hp_X]/59 mL; LEDUM PALUSTRE TWIG 10 [hp_X]/59 mL; SODIUM CARBONATE 10 [hp_X]/59 mL; STRYCHNOS NUX-VOMICA SEED 10 [hp_X]/59 mL; URTICA URENS 10 [hp_X]/59 mL
INACTIVE INGREDIENTS: WATER; ANHYDROUS CITRIC ACID; POTASSIUM SORBATE

Gout Symptom Relief™

ACTIVE INGREDIENT

Drug Facts__________________________________________________________________________________________________________

HPUS active ingredients: Ammonium phosphoricum, Belladonna, Colchicum autumnale, Formicum acidum, Fraxinus excelsior, Ledum palustre, Natrum carbonicum, Nux vomica, Urtica urens. Equal volumes of each ingredient in 10X, 30X, 100X, 1M, LM1, LM2, LM3 potencies.

INDICATIONS AND USAGE

Uses for temporary relief of pain in the foot, heel, toes and joints including: swelling, burning, itching, tingling, tearing pains, throbbing, cramps, shooting pains.

Inactive Ingredients:

Bio-Energetically Enhanced™ pure water, citric acid and potassium sorbate.

Warnings

- Stop use and ask your doctor if symptoms persist or worsen.
- If pregnant or breast-feeding, take only on advice of a healthcare professional.

- Keep out of reach of children.

Directions

- Initially, depress pump until primed.
- Spray one dose directly into mouth.
- Adults 12 and up: 3 sprays 3 times per day.
- Use additionally as needed, up to 6 times per day.

OTHER SAFETY INFORMATION

Tamper resistant for your protection. Use only if safety seal is intact.

PURPOSE

Uses for temporary relief of pain in the foot, heel, toes and joints including:

- swelling
- burning
- itching
- tingling
- tearing pains
- throbbing
- cramps
- shooting pains